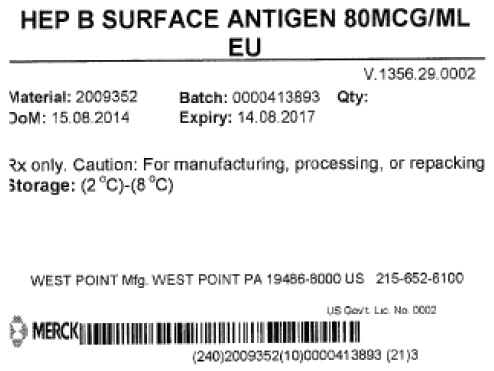 DRUG LABEL: Hepatitis B Surface Antigen
NDC: 69806-0002 | Form: LIQUID
Manufacturer: Merck Sharp & Dohme Corp.
Category: other | Type: LICENSED VACCINE BULK INTERMEDIATE LABEL
Date: 20150805

ACTIVE INGREDIENTS: HEPATITIS B VIRUS SUBTYPE ADW HBSAG SURFACE PROTEIN ANTIGEN 1 g/1 g

HEP B SURFACE ANTIGEN 80MCG/ML EU

PRINCIPAL DISPLAY PANEL - Shipping Label

HEP B SURFACE ANTIGEN 80MCG/ML
EU

V.1356.29.0002

Material: 2009352
DoM: 15.08.2014

Batch: 0000413893
Expiry: 14.08.2017

Qty:

Rx only. Caution: For manufacturing, processing, or repacking

Storage: (2 °C)-(8 °C)

WEST POINT Mfg. WEST POINT PA 19486-8000 US 215-652-6100

US Gov't Lic No. 0002

MERCK